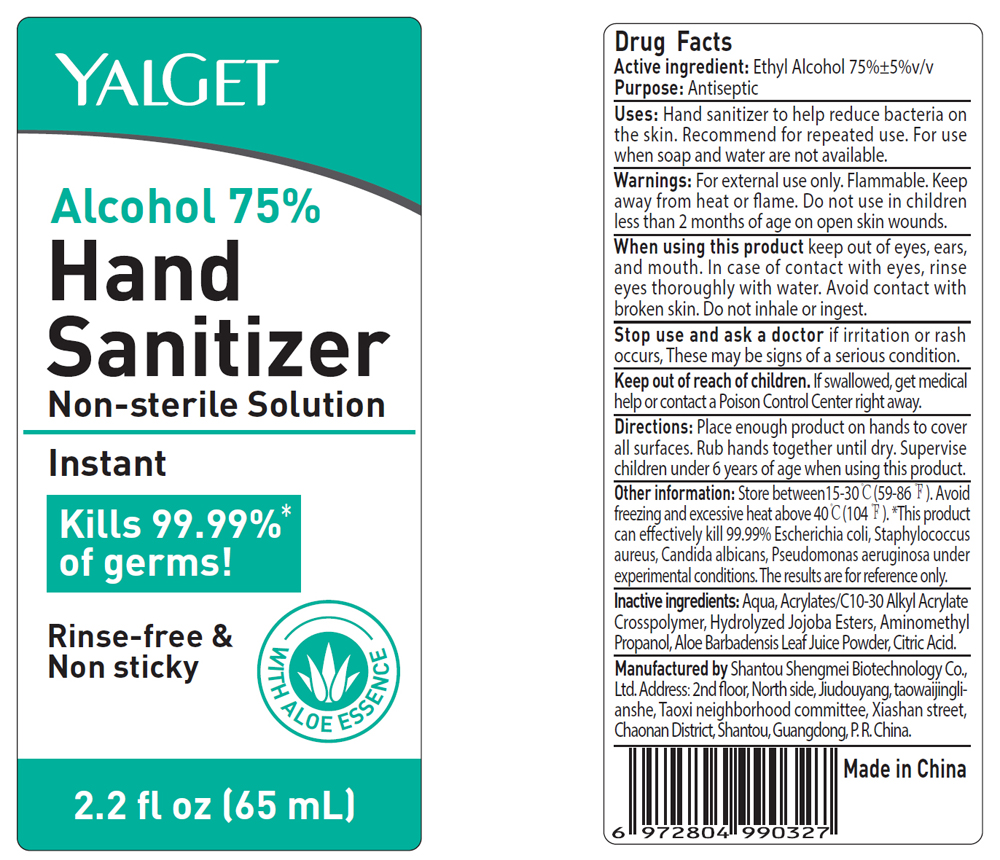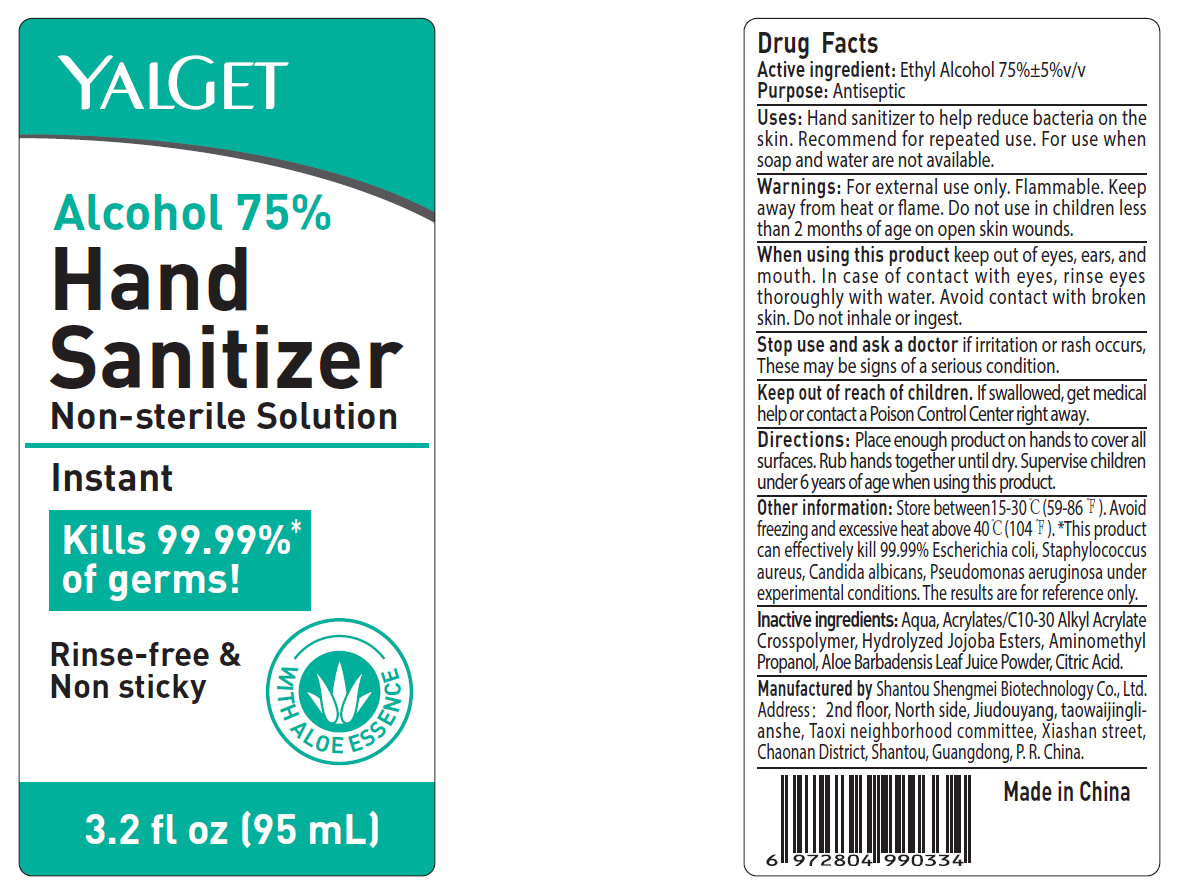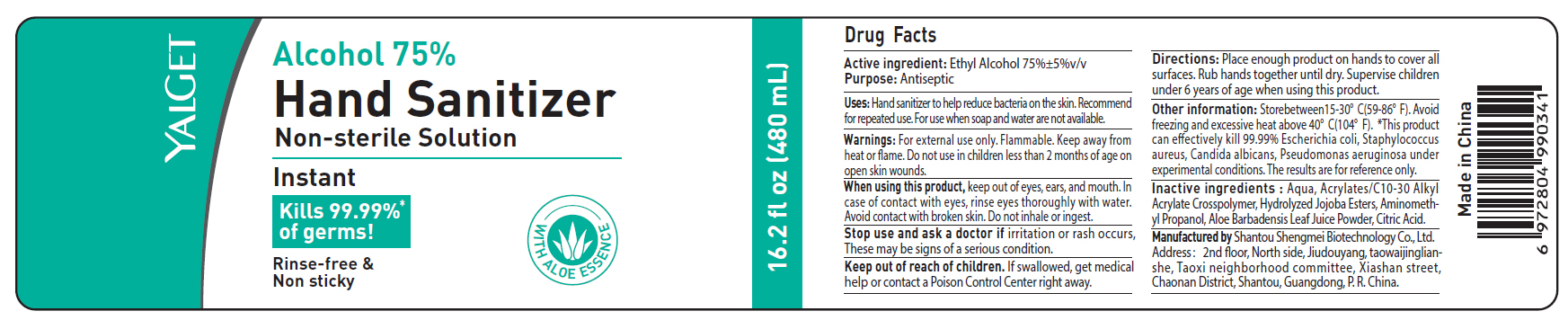 DRUG LABEL: YALGET Hand Sanitizer Non-sterile
NDC: 55450-003 | Form: GEL
Manufacturer: Shantou Shengmei Biotechnology Co., Ltd.
Category: otc | Type: HUMAN OTC DRUG LABEL
Date: 20200417

ACTIVE INGREDIENTS: ALCOHOL 75 mL/100 mL
INACTIVE INGREDIENTS: CARBOMER INTERPOLYMER TYPE A (55000 CPS); HYDROLYZED JOJOBA ESTERS (ACID FORM); AMINOMETHYLPROPANOL; ALOE VERA LEAF; CITRIC ACID MONOHYDRATE; WATER

YALGET Alcohol 75%

ACTIVE INGREDIENT

Alcohol 75% v/v. Purpose: Antiseptic

PURPOSE

Antiseptic, Hand Sanitizer

INDICATIONS AND USAGE

Hand sanitizer to help reduce bacteria on the skin. Recommend for repeated use. For use when soap and water are not available.

WARNINGS

For external use only. Flammable. Keep away from heat or flame. Do not use in children less than 2 months of age on open skin wounds.

WHEN USING

Keep out of eyes, ears, and mouth. In case of contact with eyes, rinse eyes thoroughly with water. Avoid contact with broken skin. Do not inhale or ingest.

Stop use and ask a doctor if irritation or rash occurs. These may be signs of a serious condition.

keep out of reach of children. If sallowed, get medical help or contact a Poison Control Center right away.

DOSAGE AND ADMINISTRATION

Place enough product on hands to cover all surfaces. Rub hands together until dry. Supervise children under 6 years of age when using this product.

OTHER SAFETY INFORMATION

Store between 15-30C (59-86F). Avoid freezing and excessive heat above 40C (104F).

This product can effectively kill 99.99% Escherichia coli, Staphylococcus aureus, Candida albicans, Pseudomonas aeruginosa under experimental conditions. The results are for reference only.

INACTIVE INGREDIENT

Aqua, Acrylates/C10-30 Alkyl Acrylate Crosspolymer, Hydrolyzed Jojoba Esters, Aminomethyl Propanol,Aloe Barbadensis Leaf Juice Powder, Citric Acid

PACKAGE LABEL

55450-003-01 65mL

55450-003-02 95mL

55450-003-03 480mL